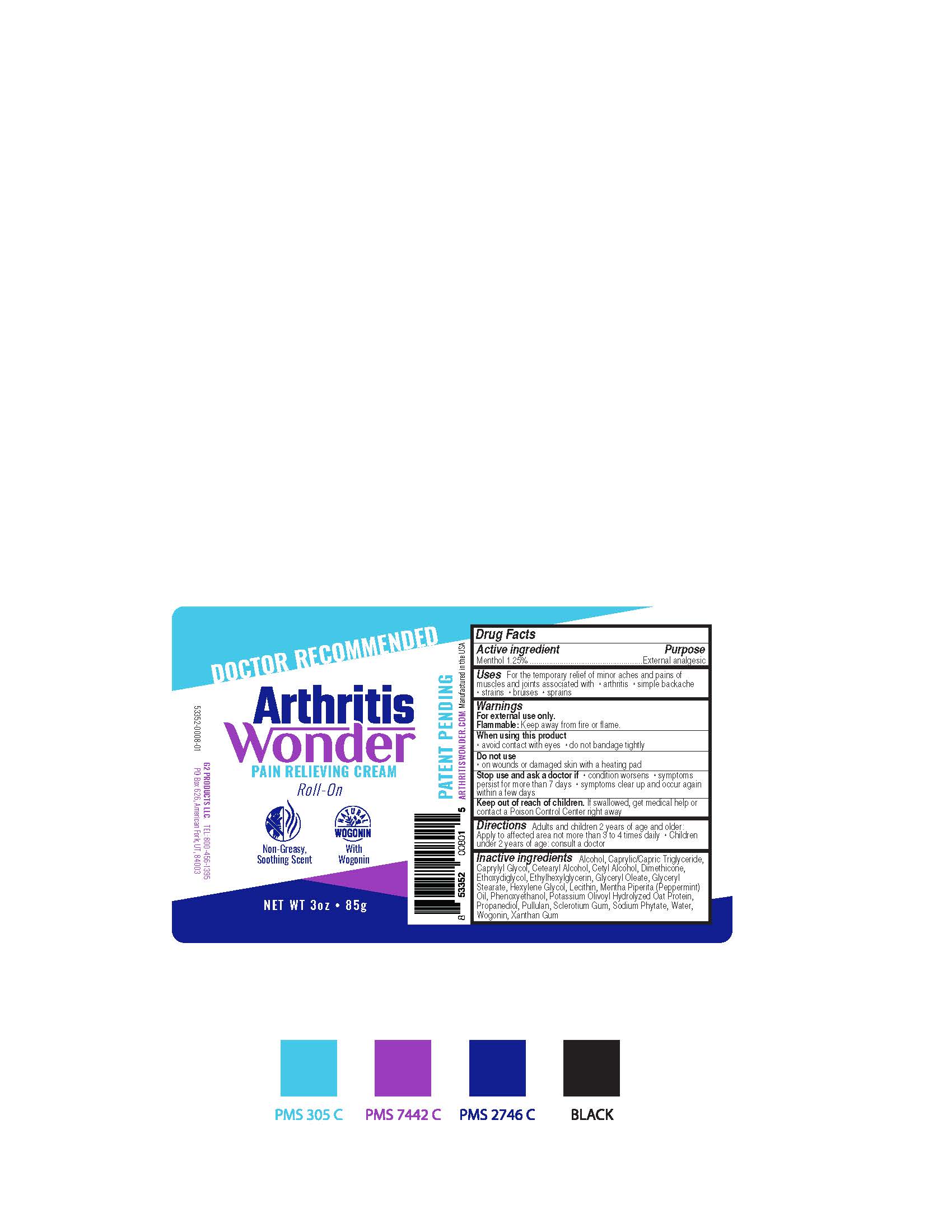 DRUG LABEL: Arthritis Wonder
NDC: 71893-101 | Form: CREAM
Manufacturer: G2 Products LLC
Category: otc | Type: HUMAN OTC DRUG LABEL
Date: 20200327

ACTIVE INGREDIENTS: MENTHOL 1.4125 g/113 g
INACTIVE INGREDIENTS: DIMETHICONE; DIETHYLENE GLYCOL MONOETHYL ETHER; LECITHIN, SOYBEAN; PHENOXYETHANOL; GLYCERYL OLEATE; HEXYLENE GLYCOL; PEPPERMINT OIL; PROPANEDIOL; PULLULAN; ETHYLHEXYLGLYCERIN; WATER; WOGONIN; XANTHAN GUM; ALCOHOL; MEDIUM-CHAIN TRIGLYCERIDES; CAPRYLYL GLYCOL; CETOSTEARYL ALCOHOL; CETYL ALCOHOL; GLYCERYL MONOSTEARATE; CLAVICEPS PURPUREA SCLEROTIUM; HEXASODIUM PHYTATE

Arthritis Wonder

Active ingredient

Menthol 1.25%

Purpose

External analgesic

Uses

For the temporary relief of minor aches and pains of muscles and joints associated with ● arthritis ● simple backache ● strains ● bruises ● sprains

Warnings

For external use only.

Flammable: Keep away from fire or flame.

When using this product

• avoid contact with the eyes • do not bandage tightly

Do not use

● on wounds or damaged skin with a heating pad

Stop use and ask a doctor if

• condition worsens • symptoms persist for more than 7 days • symptoms clear up and occur again within a few days

Keep out of the reach of children

If swallowed, get medical help or contact a Poison Control Center right away

Directions

• Adults and children 2 years of age and older: Apply to affected area not more than 3 to 4 times daily • Children under 2 years of age: consult a doctor

Inactive ingredients:

Alcohol, Caprylic/Capric Triglyceride, Caprylyl Glycol, Cetearyl Alcohol, Cetyl Alcohol, Dimethicone, Ethoxydiglycol, Ethylhexylglycerin, Glyceryl Oleate, Glyceryl Stearate, Hexylene Glycol, Lecithin, Mentha Piperita (Peppermint) Oil, Phenoxyethanol, Potassium Olivoyl Hydrolyzed Oat Protein, Propanediol, Pullulan, Sclerotium Gum, Sodium Phytate, Water, Wogonin, Xanthan Gum.